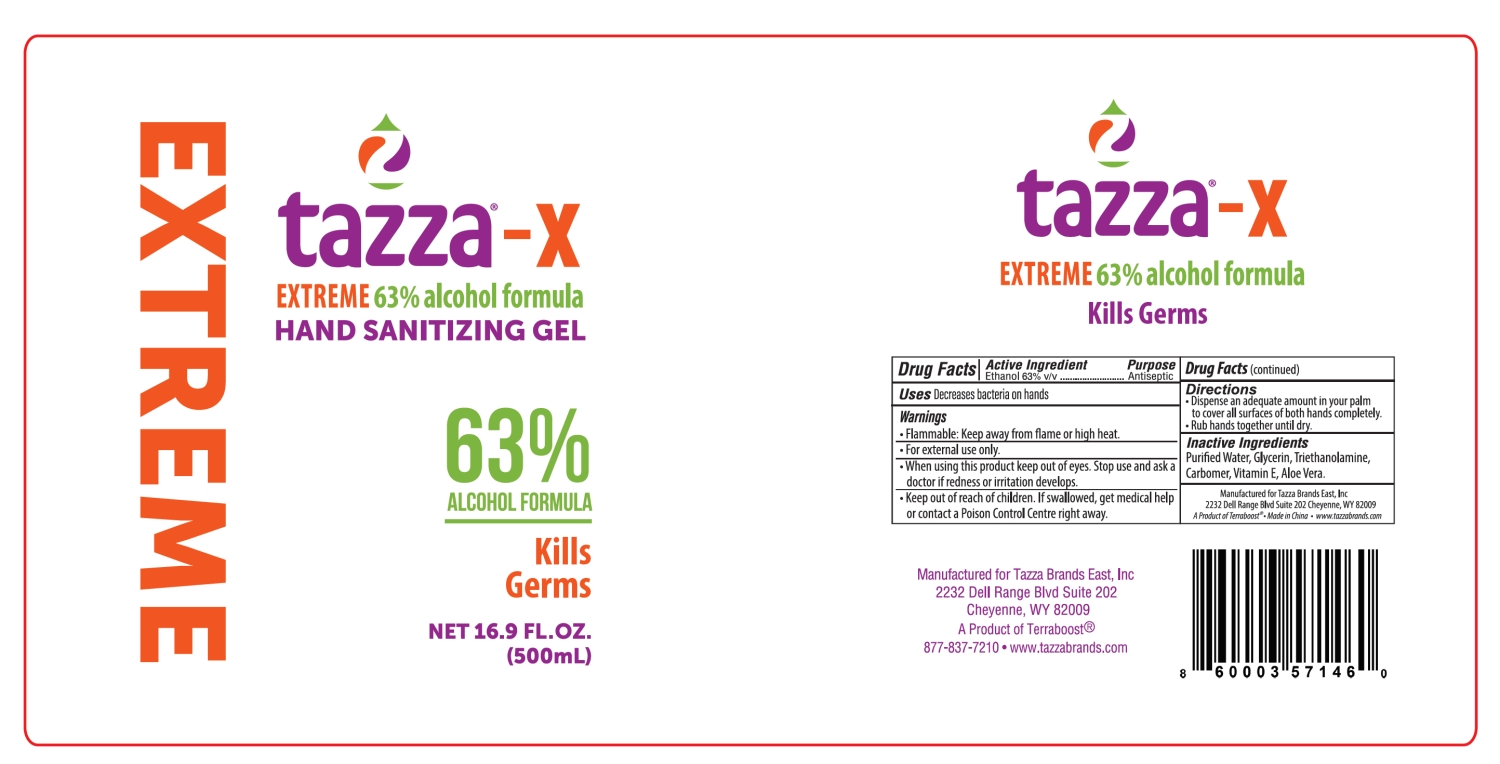 DRUG LABEL: tazza-X EXTREME 63% alcohol formula HAND SANITIZING
NDC: 76370-0034 | Form: GEL
Manufacturer: Tazza Brands East Inc.
Category: otc | Type: HUMAN OTC DRUG LABEL
Date: 20251224

ACTIVE INGREDIENTS: ALCOHOL 63 mL/100 mL
INACTIVE INGREDIENTS: TRIETHANOLAMINE; .ALPHA.-TOCOPHEROL; CARBOMER; GLYCERIN; ALOE VERA LEAF; WATER

76370-0034 tazza-X EXTREME 63% alcohol formula HAND SANITIZING GEL

Active Ingredient

Ethanol 63% v/v

Purpose

Antiseptic

INDICATIONS AND USAGE

Uses Decreases bacteria on hands

Warnings

· Flammable: Keep away from flame or high heat.

· For external use only.

· When using this product keep out of eyes. Stop use and ask a

doctor if redness or irritation develops.

· Keep out of reach of children. If swallowed, get medical help

or contact a Poison Control Center right away.

Directions

· Dispense an adequate amount in your palm

to cover all surfaces of both hands completely.

· Rub hands together until dry.

Inactive Ingredients

Purified Water, Glycerin, Triethanolamine,

Carbomer, Vitamin E, Aloe Vera.

PACKAGE LABEL

NET 16.9 FL. OZ.
(500ML)
NDC: 76370-0034-0